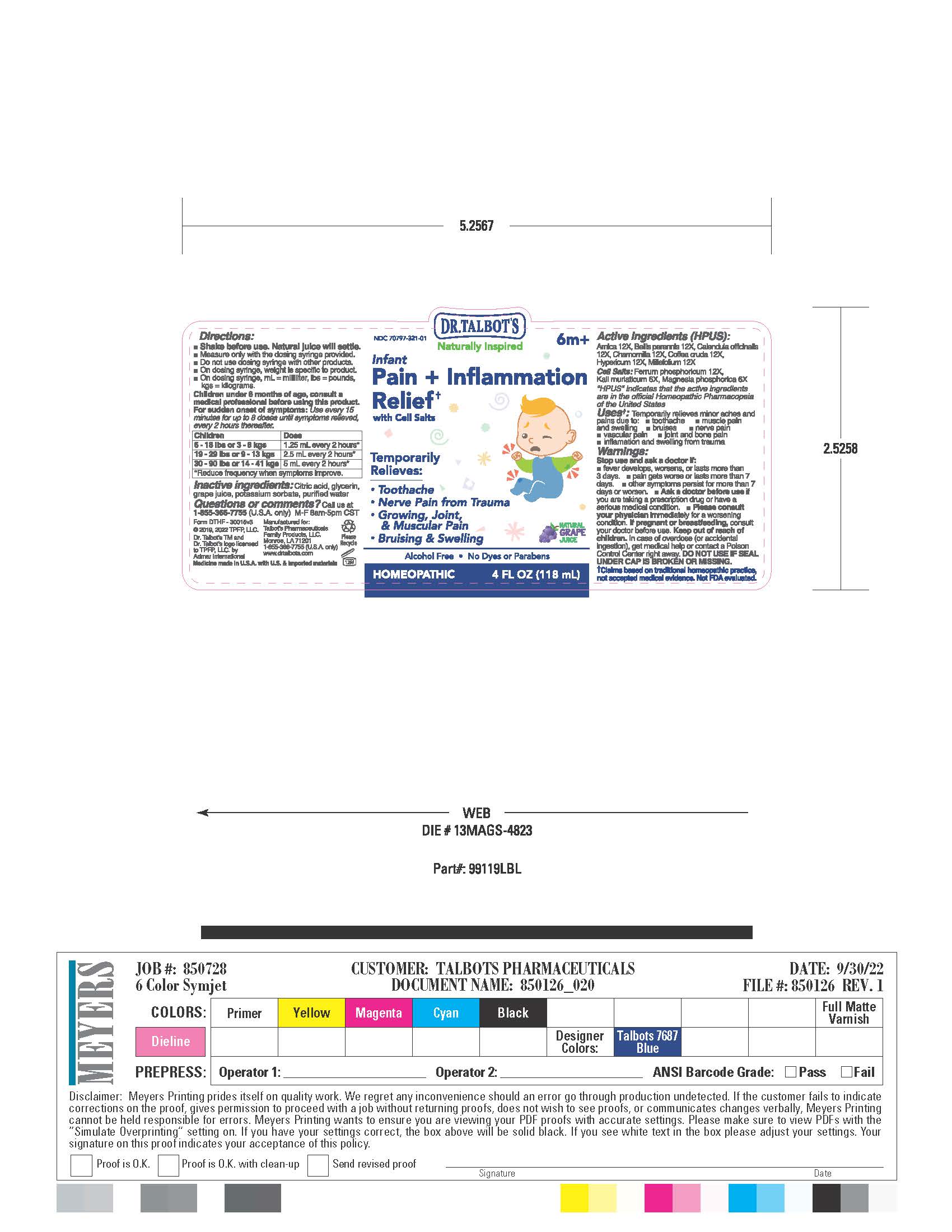 DRUG LABEL: Dr Talbots Infant Pain  Inflamtion Relief
NDC: 70797-321 | Form: LIQUID
Manufacturer: Talbot’s Pharmaceuticals Family Products, LLC.
Category: homeopathic | Type: HUMAN OTC DRUG LABEL
Date: 20220912

ACTIVE INGREDIENTS: HYPERICUM PERFORATUM 12 [hp_X]/118 mL; FERROSOFERRIC PHOSPHATE 12 [hp_X]/118 mL; ARNICA MONTANA 12 [hp_X]/118 mL; BELLIS PERENNIS 12 [hp_X]/118 mL; POTASSIUM CHLORIDE 6 [hp_X]/118 mL; MAGNESIUM PHOSPHATE, DIBASIC TRIHYDRATE 6 [hp_X]/118 mL; MATRICARIA CHAMOMILLA 12 [hp_X]/118 mL; CALENDULA OFFICINALIS FLOWERING TOP 12 [hp_X]/118 mL; ARABICA COFFEE BEAN 12 [hp_X]/118 mL
INACTIVE INGREDIENTS: CONCORD GRAPE JUICE; POTASSIUM SORBATE; GLYCERIN; WATER; CITRIC ACID MONOHYDRATE

ACTIVE INGREDIENTS

Active ingredients (HPUS)

Arnica 12X

Bellis perennis 12X

Calendula officinalis 12X

Chamomilla 12X

Coffea cruda 12X

Hypericum 12X

Millefolium 12X

Cell Salts

Ferrum phosphoricum 12X

Kali muriaticum 6X

Magnesia phosphorica 6X

INACTIVE INGREDIENTS

Citric acid, glycerin, grape juice, potassium
sorbate, purified water

PREGNANCY

Pregnant or breastfeeding

If pregnant or breastfeeding, consult your doctor before use.

Ask a doctor before use if you are taking a prescription
drug or have a serious medical condition.

Please consult your physician immediately for a worsening condition.

QUESTIONS

Questions or comments?
Call us at 1-855-366-7755 (U.S.A. only)
M-F 8am-5pm CST

Purpose

Temporarily Relieves:

- Toothache
- Nerve Pain from Trauma
- Growing, Joint, & Muscular Pain
- Bruising & SWelling

Usage

Uses:

Temporarily relieves minor aches and pains due to:

- toothache
- muscle pain and swelling
- bruises
- nerve pain
- vascular pain
- joint and bone pain
- inflamation and swelling from trauma

Dosage

Children under 6 months of age, consult a medical professional before using this product.

For sudden onset of symptoms: Use every 15 minutes for upto 8 doses until symtoms relieved, every 2 hours thereafter.

Children Dose
6 - 18 lbs or 3 - 8 kgs 1.25 mL every 2 hours*
19 - 29 lbs or 9 - 13 kgs 2.5 mL every 2 hours*
30 - 90 lbs or 14 - 41 kgs 5 mL every 2 hours*
*Reduce frequency when symptoms improve.

Warning

Warnings:

Stop use and ask a doctor if:

- fever develops, worsens, or lasts more than 3 days
- pain gets worse or lasts more than 7 days
- other symtoms persist for more than 7 days or worsen

Keep out of reach of children. In case of overdose (or accidental ingestion), get medical help or contact a Poison Control Center right away. DO NOT USE IF SEAL UNDER CAP IS BROKEN OR MISSING.

Principal Display Panel